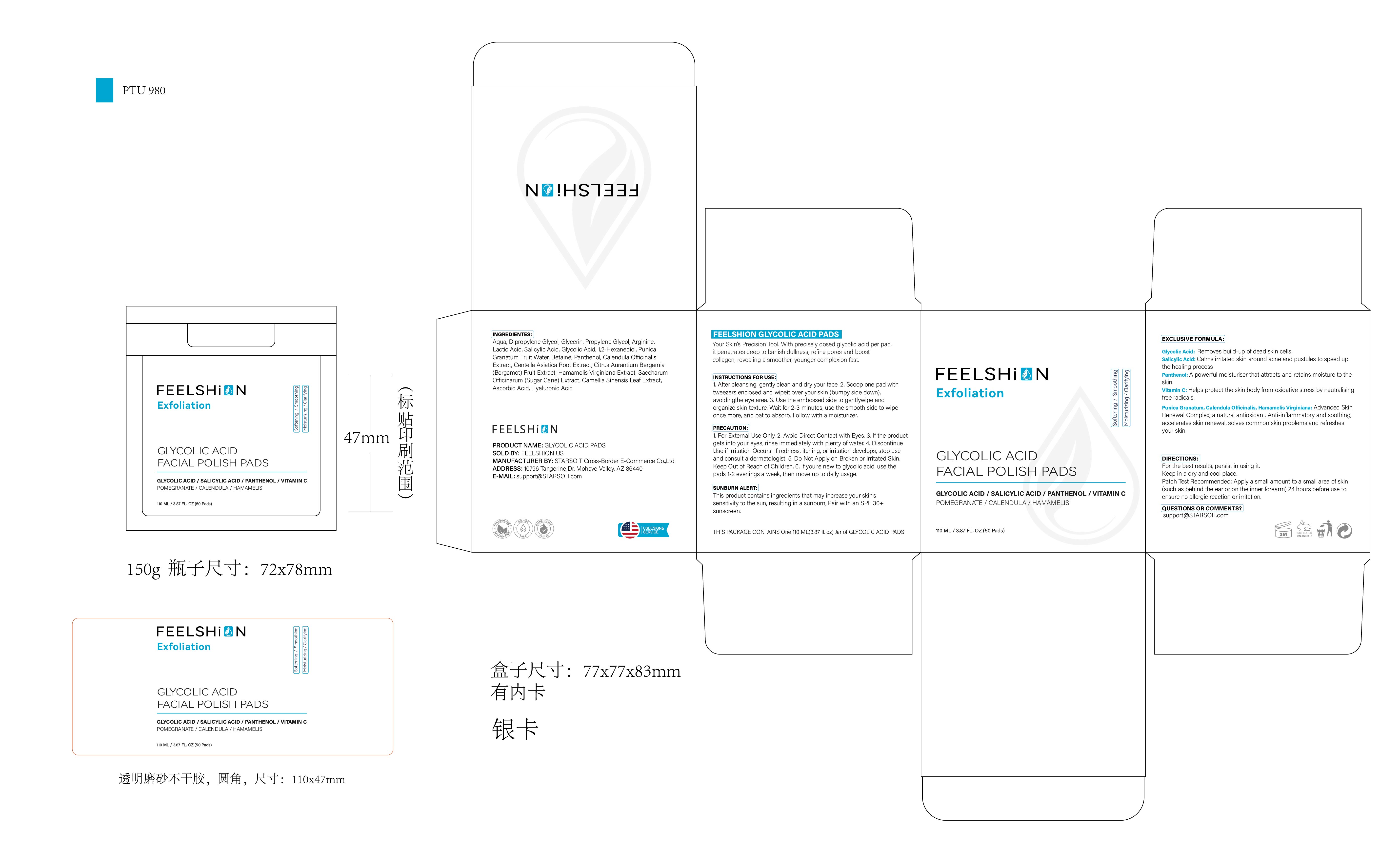 DRUG LABEL: FEELSHION Glycolic Acid Exfoliating Face Pads
NDC: 85212-0009 | Form: PATCH
Manufacturer: Beijing JUNGE Technology Co., Ltd.
Category: otc | Type: HUMAN OTC DRUG LABEL
Date: 20250219

ACTIVE INGREDIENTS: ARGININE 2 g/100 mL; GLYCOLIC ACID 1 g/100 mL; SALICYLIC ACID 1 g/100 mL; PROPYLENE GLYCOL 3 g/100 mL; LACTIC ACID 2 g/100 mL
INACTIVE INGREDIENTS: HYALURONIC ACID 0.1 mL/100 mL; 1,2-HEXANEDIOL 1 mL/100 mL; PUNICA GRANATUM FRUIT JUICE 0.5 g/100 mL; CALENDULA OFFICINALIS WHOLE 0.2 mL/100 mL; AQUA 78.3 mL/100 mL; CENTELLA ASIATICA ROOT 0.2 mL/100 mL; BETAINE 0.5 mL/100 mL; CAMELLIA SINENSIS LEAF 0.1 mL/100 mL; GLYCERIN 3 mL/100 mL; PANTHENOL 0.5 mL/100 mL; CITRUS AURANTIUM BERGAMIA (BERGAMOT) FRUIT OIL 0.2 mL/100 mL; HAMAMELIS VIRGINIANA (WITCH HAZEL) LEAF WATER 0.2 mL/100 mL; SACCHARUM OFFICINARUM WHOLE 0.1 mL/100 mL; ASCORBIC ACID 0.1 mL/100 mL; DIPROPYLENE GLYCOL 6 mL/100 mL

DOSAGE AND ADMINISTRATION

110 ML / 3.87 FL.0Z (50 Pads)

WARNINGS

PRECAUTION:
1.For External Use Only. 2.Avoid Direct Contact with Eyes. 3.If the product gets into your eyes, rinse immediately with plenty of water. 4.Discontinue Use if Irritation Occurs: If redness, itching, or irritation develops, stop use and consult a dermatologist. 5.Do Not Apply on Broken or Irritated Skin. Keep Out of Reach of Children. 6.If you're new to glycolic acid, use the pads 1-2 evenings a week, then move up to daily usage.
SUNBURN ALERT:
This product contains ingredients that may increase your skin's sensitivity to the sun, resulting in a sunburn, Pair with an SPF 30+ sunscreen.

INACTIVE INGREDIENT

AQUA
DIPROPYLENE GLYCOL
GLYCERIN
1,2-HEXANEDIOL
PUNICA GRANATUM FRUIT WATER
BETAINE
PANTHENOL
CALENDULA OFFICINALIS EXTRACT
CENTELLA ASIATICA ROOT EXTRACT
CITRUS AURANTIUM BERGAMIA (BERGAMOT) FRUIT EXTRACT
HAMAMELIS VIRGINIANA (WITCH HAZEL) EXTRACT
SACCHARUM OFFICINARUM (SUGAR CANE) EXTRACT
CAMELLIA SINENSIS LEAF EXTRACT
ASCORBIC ACID
HYALURONIC ACID

INDICATIONS AND USAGE

INSTRUCTIONS FOR USE:
1.After cleansing, gently clean and dry your face.

2.Scoop one pad with tweezers enclosed and wipe it over your skin (bumpy side down), avoiding the eye area.

3.Use the embossed side to gentlywipe and organize skin texture. Wait for 2-3 minutes, use the smooth side to wipe once more, and pat to absorb. Follow with a moisturizer.

keep out of reach of children

PURPOSE

Reduce acne scars and blemishes
Even skin tone
Refine and smooth the skin’s surface
Leave the skin more radiant

ACTIVE INGREDIENT

PROPYLENE GLYCOL,ARGININE,LACTIC ACID,SALICYLIC ACID,GLYCOLIC ACID